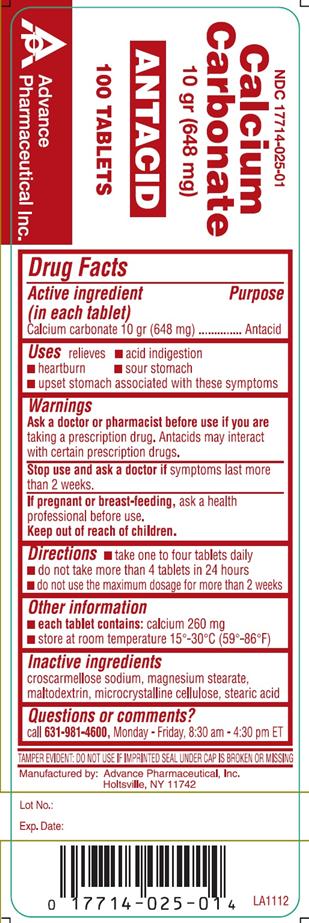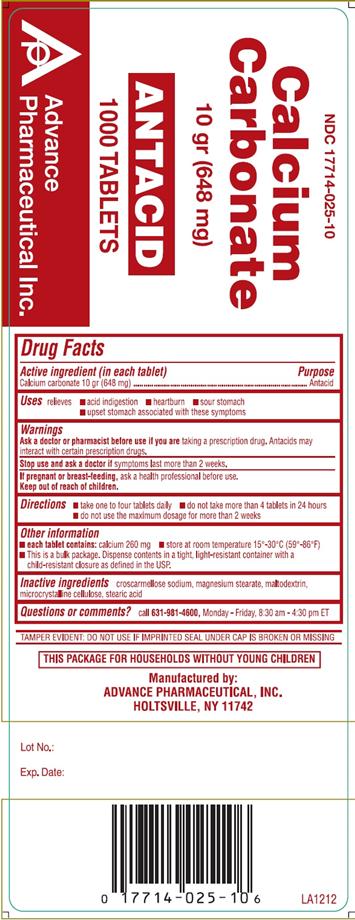 DRUG LABEL: ANTACID
NDC: 17714-025 | Form: TABLET
Manufacturer: Advance Pharmaceutical Inc.
Category: otc | Type: HUMAN OTC DRUG LABEL
Date: 20171222

ACTIVE INGREDIENTS: CALCIUM CARBONATE 648 mg/1 1
INACTIVE INGREDIENTS: CROSCARMELLOSE SODIUM; MAGNESIUM STEARATE; MALTODEXTRIN; CELLULOSE, MICROCRYSTALLINE; STEARIC ACID

Calcium Carbonate 10 gr (648 mg)

Active Ingredient

(in each tablet)

Calcium Carbonate 10 gr (648 mg)

Purpose

Antacid

Uses

relieves

- acid indigestion
- heartburn
- sour stomach
- upset stomach associated with these symptoms

Warnings

Ask a doctor or pharmacist before use if you are taking a prescription drug. Antacids may interact with certain prescription drugs.

Stop use and ask a doctor if symptoms last more than 2 weeks.

If pregnant or breast-feeding, ask a health professional before use.

Keep out of reach of children.

In case of overdose, get medical help or contact a Poison Control Center right away.

Directions

- take one to four tablets daily.
- do not take more than 4 tablets in 24 hours
- do not use the maximum dosage for more than 2 weeks

Other Information

- each tablet contains: calcium 260 mg
- store at room temperature 15-30 °C (59-86 °F)
- For 1000 Count: This is a bulk package. Dispense contents in a tight, light-resistant container with a child-resistant closure as defined in the USP.

Inactive Ingredients

Croscarmellose sodium, magnesium stearate, maltodextrin, microcrystalline cellulose, stearic acid

Questions or Comments

Call 631-981-4600, Monday-Friday, 8.30 am – 4.30 pm ET

TAMPER EVIDENT: DO NOT USE IF IMPRINTED SAFETY SEAL UNDER CAP IS BROKEN OR MISSING

Manufactured by: Advance Pharmaceutical Inc. Holtsville, NY 11742

PACKAGE LABEL.PRINCIPAL DISPLAY PANEL

Calcium Carbonate 10 gr

Antacid tablets

NDC: 17714-025-01 – 100 COUNT

NDC: 17714-025-10 – 1000 COUNT (THIS PACKAGE FOR HOUSEHOLDS WITHOUT YOUNG CHILDREN)